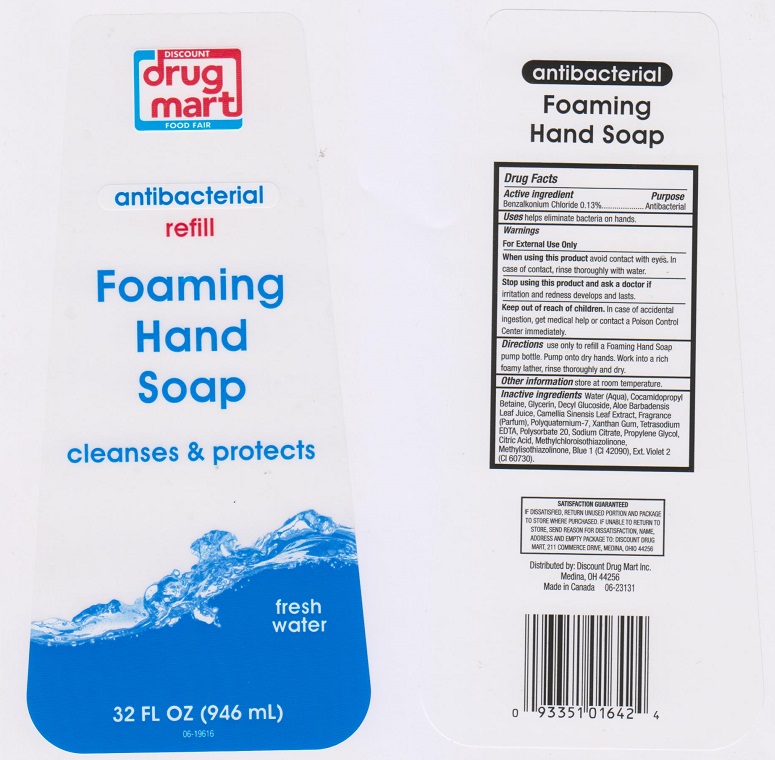 DRUG LABEL: Discount Drug Mart
NDC: 53943-114 | Form: LIQUID
Manufacturer: Discount Drug Mart
Category: otc | Type: HUMAN OTC DRUG LABEL
Date: 20170510

ACTIVE INGREDIENTS: BENZALKONIUM CHLORIDE 1.3 mg/1 mL
INACTIVE INGREDIENTS: WATER; COCAMIDOPROPYL BETAINE; GLYCERIN; DECYL GLUCOSIDE; ALOE VERA LEAF; GREEN TEA LEAF; POLYQUATERNIUM-7 (70/30 ACRYLAMIDE/DADMAC; 1600000 MW); XANTHAN GUM; EDETATE SODIUM; POLYSORBATE 20; SODIUM CITRATE; PROPYLENE GLYCOL; CITRIC ACID MONOHYDRATE; METHYLCHLOROISOTHIAZOLINONE; METHYLISOTHIAZOLINONE; FD&C BLUE NO. 1; EXT. D&C VIOLET NO. 2

Drug Facts

Active ingredient

Benzalkonium Chloride 0.13%

Purpose

Antibacterial

Uses

helps eliminate bacteria on hands.

Warnings

For external use only.

When using this product

avoid contact with eyes. In case of contact, rinse thoroughly with water.

Stop using this product and ask a doctor if

irritation and redness develops and lasts.

Keep out of reach of children.

In case of accidental ingeation, get medical help or contact a Poison Control Center immediately

Directions

use only to refill a foaming hand soap pump bottle. Pump onto dry hands. Work into a rich foamy lather, rinse thoroughly and dry.

Other information

store at room temperature

Inactive ingredients

Water (Aqua), Cocamidopropyl Betaine, Glyceri, Decyl Glucoside, Aloe Barbadensis Leaf Juice, Camellia Sinensis Leaf Extract, Fragrance (Parfum), Polyquaternium-7, Xanthan Gum, Tetrasodium EDTA, Polysorbate 20, Sodium Citrate, Propylene Glycol, Citric Acid, Methylchloroisothiazolinone, Methylisothiazolinone, Blue 1 (CI 42090), Ext. Violet 2 (CI 60730).